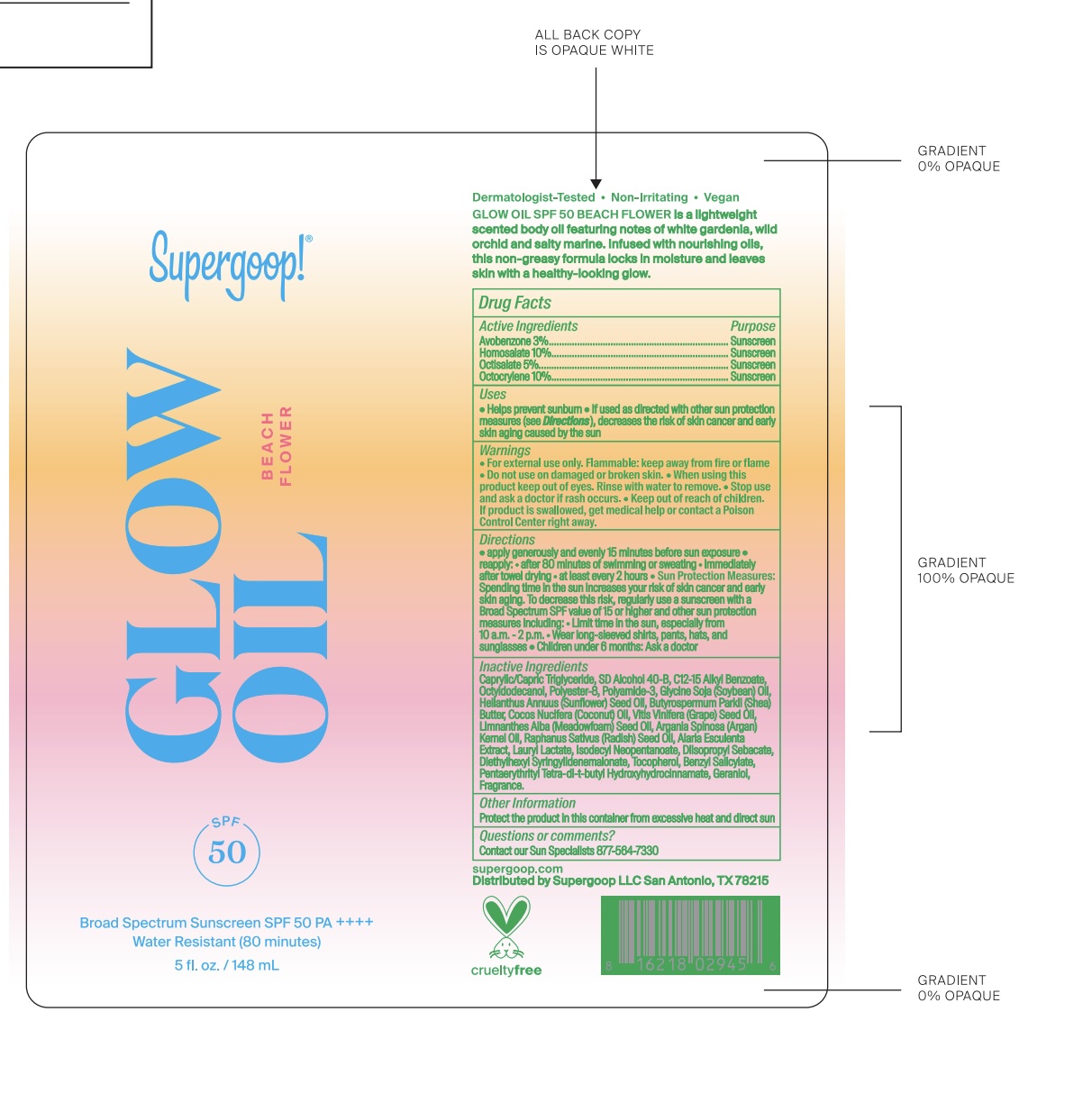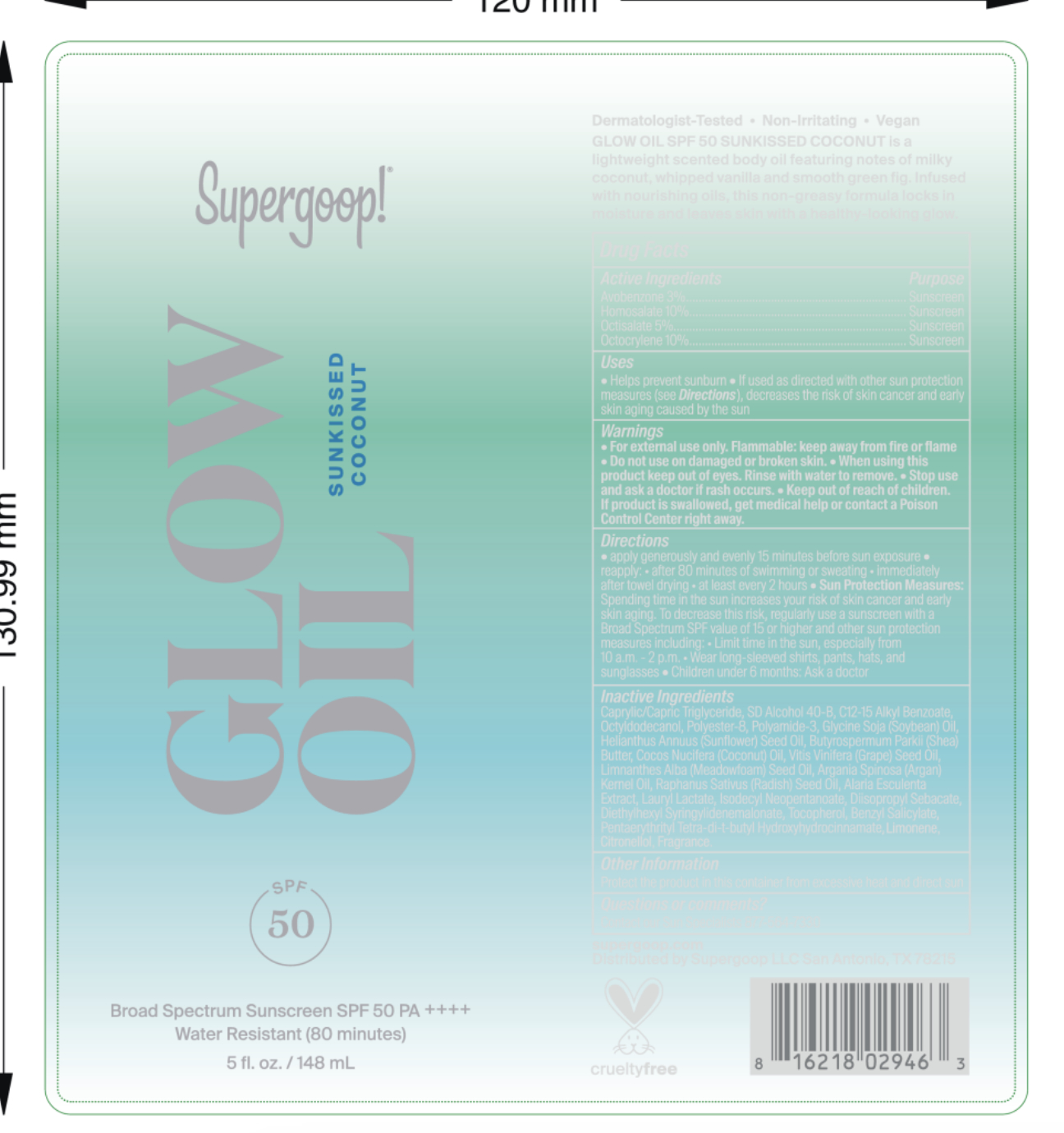 DRUG LABEL: Glow Oil SPF 50 Sunkissed Coconut
NDC: 75936-655 | Form: OIL
Manufacturer: Supergoop, LLC
Category: otc | Type: HUMAN OTC DRUG LABEL
Date: 20251217

ACTIVE INGREDIENTS: AVOBENZONE 3 g/100 mL; OCTOCRYLENE 10 g/100 mL; OCTISALATE 5 g/100 mL; HOMOSALATE 10 g/100 mL
INACTIVE INGREDIENTS: DIETHYLHEXYL SYRINGYLIDENEMALONATE; TOCOPHEROL; SOYBEAN OIL; PENTAERYTHRITOL TETRAKIS(3-(3,5-DI-TERT-BUTYL-4-HYDROXYPHENYL)PROPIONATE); DENATONIUM BENZOATE; SUNFLOWER OIL; ARGAN OIL; ALARIA ESCULENTA; SHEA BUTTER; GRAPE SEED OIL; MEADOWFOAM SEED OIL; OCTYLDODECANOL; LAURYL LACTATE; TERT-BUTYL ALCOHOL; POLYAMIDE-3 (12000 MW); COCONUT OIL; MEDIUM-CHAIN TRIGLYCERIDES; ALCOHOL; ALKYL (C12-15) BENZOATE; POLYESTER-8 (1400 MW, CYANODIPHENYLPROPENOYL CAPPED); ISODECYL NEOPENTANOATE; DIISOPROPYL SEBACATE; COUMARIN; BENZYL SALICYLATE; RAPHANUS SATIVUS VAR. SATIVUS SEED; GERANIOL; VANILLIN; DIPTERYX ODORATA SEED; TRIETHYL CITRATE; .GAMMA.-OCTALACTONE; PHENETHYL ALCOHOL; DIPTEROCARPUS TURBINATUS WOOD OIL; 3-HEXENOL; BENZYL ALCOHOL; CITRUS LIMON (LEMON) PEEL OIL; IONONE; LIMONENE, (+)-; LINALOOL, (+)-; CITRAL; BENZYL BENZOATE; CITRONELLOL; EUGENOL

Glow Oil SPF 50

Active Ingredients Purpose

Avobenzone 3% Sunscreen

Homosalate 10% Sunscreen

Octisalate 5% Sunscreen

Octocrylene 10% Sunscreen

Uses

- Helps Prevent Sunburn
- If used as directed with other sun protection measures (see Directions), decreases the risk of skin cancer and early skin aging caused by the sun.

Keep out of reach of children

If product is swallowed, get medical help or contact a poison Control Center right away

Stop use and ask a doctor if rash occurs

Warnings

Do not use on damaged or broken skin
When using this product keep out of eyes. Rinse with water to remove
For external use only

Directions

- Apply generously and evenly 15 minutes before sun exposure
- Reapply
- at least every 2 hours.
- after 80 minutes if swimming or sweating
- Sun Protection Measures Spending time in the sun increases your risk of

skin cancer and early skin aging. To decrease this risk, regularly use a
sunscreen with a Broad-Spectrum SPF value of 15 or higher and other sun
protection measures including: • limit your time in the sun, especially from 10
a.m. – 2 p.m. • wear long-sleeved shirts, pants, hats, and sunglasses

- Children under 6 months of age: ask a doctor.

INACTIVE INGREDIENT

Caprylic/Capric Triglyceride, SD Alcohol 40-B, C12-15 Alkyl Benzoate, Octyldodecanol, Polyester-8, Polyamide-3, Glycine Soja (Soybean) Oil, Helianthus Annuus (Sunflower) Seed Oil, Butyrospermum Parkii (Shea) Butter, Cocos Nucifera (Coconut) Oil, Vitis Vinifera (Grape) Seed Oil, Limnanthes Alba (Meadowfoam) Seed Oil, Argania Spinosa (Argan) Kernel Oil, Raphanus Sativus (Radish) Seed Oil, Alaria Esculenta Extract, Lauryl Lactate, Isodecyl Neopentanoate, Diisopropyl Sebacate, Diethylhexyl Syringylidenemalonate, Tocopherol, Benzyl Salicylate, Pentaerythrityl Tetra-di-t-butyl Hydroxyhydrocinnamate, Geraniol, Fragrance.

PACKAGE LABEL

Supergoop!

Glow Oil SPF 50

Broad Spectrum Sunscreen SPF 50

Sunkissed Coconut / Beach Flower

Water Resistant (80 minutes) 5 fl. oz./ 148 ml